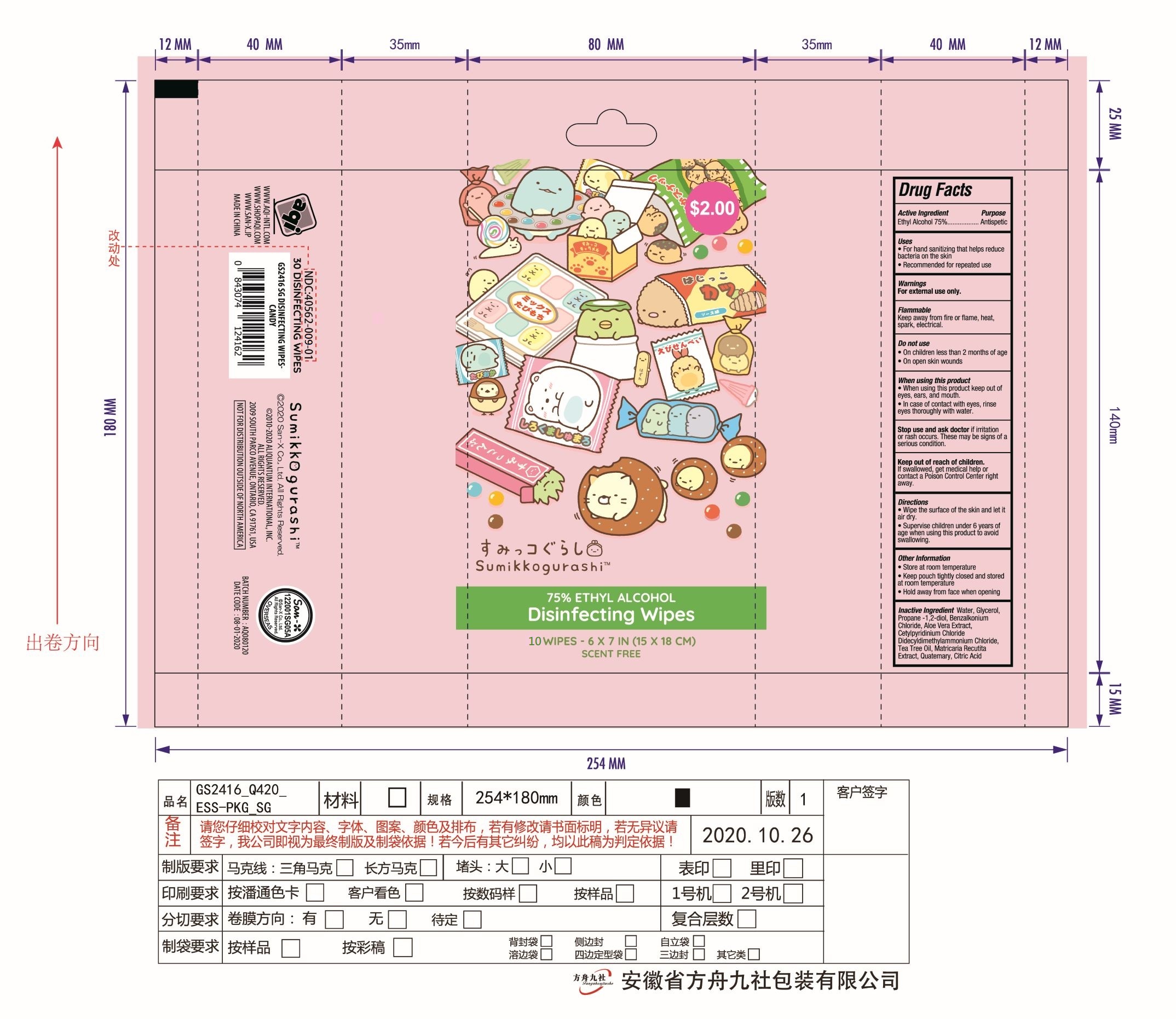 DRUG LABEL: 75% Alcohol Wipes
NDC: 40562-009 | Form: CLOTH
Manufacturer: Anhui Hanbon Daily Chemical Co., Ltd.
Category: otc | Type: HUMAN OTC DRUG LABEL
Date: 20220123

ACTIVE INGREDIENTS: ALCOHOL 75 mL/100 mL
INACTIVE INGREDIENTS: ALOE VERA LEAF; CETYLPYRIDINIUM CHLORIDE ANHYDROUS; BENZALKONIUM CHLORIDE; CHAMOMILE; DIDECYLDIMONIUM CHLORIDE; N-ALKYL ETHYLBENZYL DIMETHYL AMMONIUM CHLORIDE (C12-C14); GLYCERIN; PROPYLENE GLYCOL; WATER; TEA TREE OIL; ANHYDROUS CITRIC ACID

Hanbon 75% Alcohol Wipes
Update label.jpg

Active Ingredient(s)

Ethyl Alcohol 75% v/v.

Purpose

Antiseptic

Use

- For hand sanitizing that helps reduce bacteria on the skin.
- Recommended for repeated use.

Warnings

- For external use only.
- Flammable, Keep away from fire or flame, heat, spark, electrical.

Do not use

- On children less than 2 months of age.
- On open skin wounds.

- When using this product keep out of eyes, ears, and mouth.
- In case of contact with eyes, rinse eyes thoroughly with water.

Stop use and ask a doctor if irritation or rash occurs. These may be signs of a serious condition.

Keep out of reach of children. If swallowed, get medical help or contact a Poison Control Center right away.

Directions

- Wipe the surface of the skin and let it air dry.
- Supervise children under 6 years of age when using this product to avoid swallowing.

Other information

- Store at room temperature.
- Keep pouch tightly closed and stored at room temperature.
- Hold away from face when opening.

Inactive ingredients

Water, Glycerol, Propane -1,2-diol, Benzalkonium Chloride, Aloe Vera Extract, Cetylpyridinium Chloride, Didecyldimethylammonium Chloride, Tea Tree Oil, Matricaria Recutita Extract, Quaternary, Citric Acid.

Package Label - Principal Display Panel

10 PATCH in 1 PACKET NDC: 40562-009-01

50 PATCH in 1 PACKET NDC: 40562-009-02

40 PATCH in 1 PACKET NDC: 40562-009-03